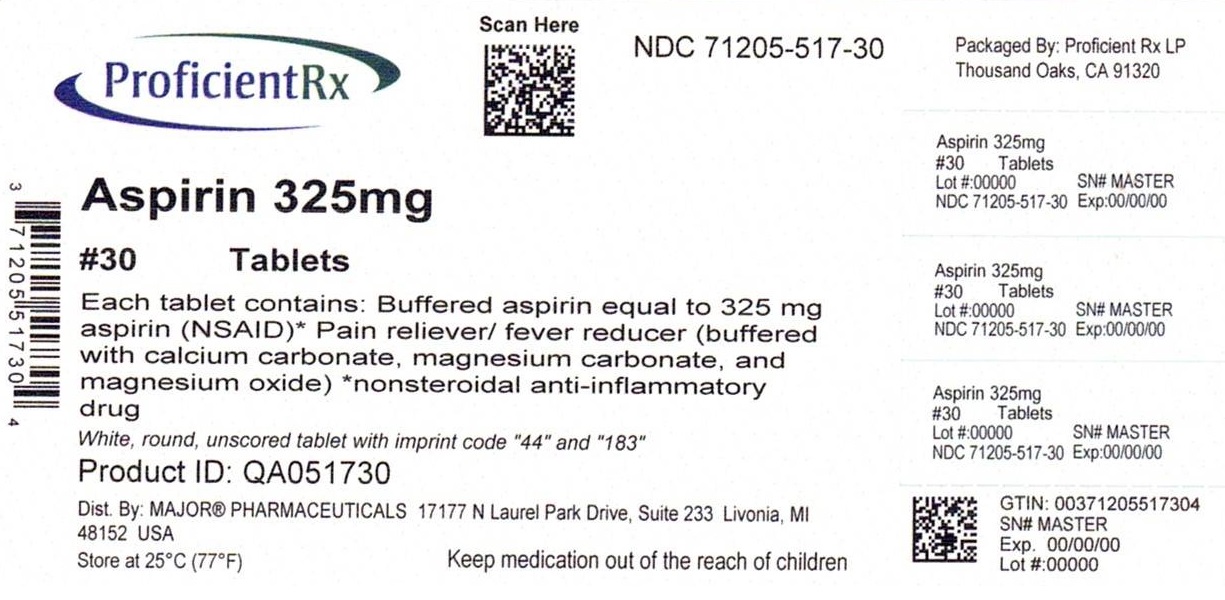 DRUG LABEL: Tri-Buffered Aspirin
NDC: 71205-517 | Form: TABLET, FILM COATED
Manufacturer: Proficient Rx LP
Category: otc | Type: HUMAN OTC DRUG LABEL
Date: 20231001

ACTIVE INGREDIENTS: ASPIRIN 325 mg/1 1
INACTIVE INGREDIENTS: ANHYDROUS CITRIC ACID; HYPROMELLOSE, UNSPECIFIED; MICROCRYSTALLINE CELLULOSE; DIMETHICONE 410; SODIUM LAURYL SULFATE; TALC; TITANIUM DIOXIDE; POLYETHYLENE GLYCOL, UNSPECIFIED; PROPYLENE GLYCOL; SHELLAC; STARCH, CORN; SODIUM PHOSPHATE, DIBASIC, ANHYDROUS; SILICON DIOXIDE; HYDROGENATED COTTONSEED OIL

Major 44-183

Active ingredient (in each tablet)

Buffered aspirin equal to
325 mg aspirin (NSAID)*
(buffered with calcium carbonate, magnesium carbonate, and magnesium oxide)
*nonsteroidal anti-inflammatory drug

Purpose

Pain reliever/fever reducer

Uses

- temporarily relieves minor aches and pains associated with:
  - toothache
  - minor pain of arthritis
  - backache
  - the common cold
  - headache
  - muscular aches
  - premenstrual & menstrual cramps
- temporarily reduces fever

Warnings

Reye's syndrome: Children and teenagers who have or are recovering from chicken pox or flu-like symptoms should not use this product. When using this product, if changes in behavior with nausea and vomiting occur, consult a doctor because these symptoms could be an early sign of Reye's syndrome, a rare but serious illness.

Allergy alert: Aspirin may cause a severe allergic reaction, which may include:

- hives
- facial swelling
- shock
- asthma (wheezing)

Stomach bleeding warning: This product contains an NSAID, which may cause severe stomach bleeding. The chance is higher if you

- have had stomach ulcers or bleeding problems
- have 3 or more alcoholic drinks every day while using this product
- are age 60 or older
- take a blood thinning (anticoagulant) or steroid drug
- take other drugs containing prescription or nonprescription NSAIDs [aspirin, ibuprofen, naproxen, or others]
- take more or for a longer time than directed

Do not use

- if you are allergic to aspirin or any other pain reliever/fever reducer
- if you have ever had an allergic reaction to this product or any of its ingredients

Ask a doctor before use if

- stomach bleeding warning applies to you
- you have a history of stomach problems, such as heartburn
- you have asthma
- you are taking a diuretic
- you have high blood pressure, heart disease, liver cirrhosis, or kidney disease

Ask a doctor or pharmacist before use if you are

taking a prescription drug for

- gout
- arthritis
- diabetes

Stop use and ask a doctor if

- an allergic reaction occurs. Seek medical help right away.
- you experience any of the following signs of stomach bleeding:
  - feel faint
  - vomit blood
  - have bloody or black stools
  - have stomach pain that does not get better
- ringing in the ears or a loss of hearing occurs
- pain gets worse or lasts more than 10 days
- fever gets worse or lasts more than 3 days
- redness or swelling is present
- new symptoms occur

These could be signs of a serious condition.

If pregnant or breast-feeding,

ask a health professional before use. It is especially important not to use aspirin during the last 3 months of pregnancy unless definitely directed to do so by a doctor because it may cause problems in the unborn child or complications during delivery.

Keep out of reach of children.

In case of overdose, get medical help or contact a Poison Control Center (1-800-222-1222) right away.

Directions

- drink a full glass of water with each dose
- adults and children 12 years and over: take 2 tablets every 4 hours not to exceed 12 tablets in 24 hours unless directed by a doctor
- children under 12 years: do not use unless directed by a doctor

Other information

- each tablet contains: calcium 35 mg and magnesium 40 mg
- store at 25ºC (77ºF); excursions permitted between 15º-30ºC (59º-86ºF)
- see end flap for expiration date and lot number

Inactive ingredients

anhydrous citric acid, corn starch, dibasic sodium phosphate anhydrous, hydrogenated vegetable oil, hypromellose, microcrystalline cellulose, polyethylene glycol, propylene glycol, shellac wax, simethicone, sodium lauryl sulfate, talc, titanium dioxide

Questions or comments?

(800) 616-2471

Principal Display Panel

NDC 71205-517-30

Compare to the active ingredient in BUFFERIN®†

TRI-BUFFERED
ASPIRIN
325 mg

pain reliever/fever reducer (NSAID)

30 TABLETS

†This product is not manufactured or distributed by Dr. Reddy's Laboratories Inc., owner of the registered trademark Bufferin®.
50844 REV0318M18312

Distributed by MAJOR® PHARMACEUTICALS
17177 N Laurel Park Drive, Suite 233
Livonia, MI 48152 USA

Repackaged by Proficient Rx LP
Thousand Oaks, CA 91320

M-17
Re-order No. 700594 Rev. 07/18

TAMPER EVIDENT: DO NOT USE IF IMPRINTED SAFETY SEAL UNDER CAP IS BROKEN OR MISSING